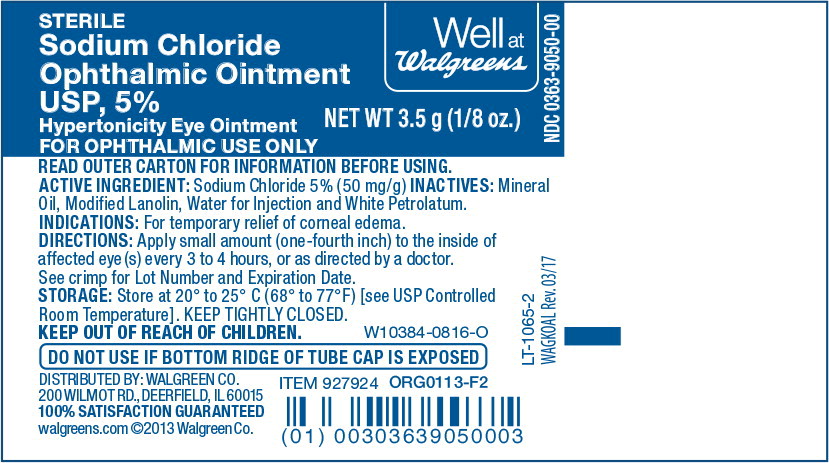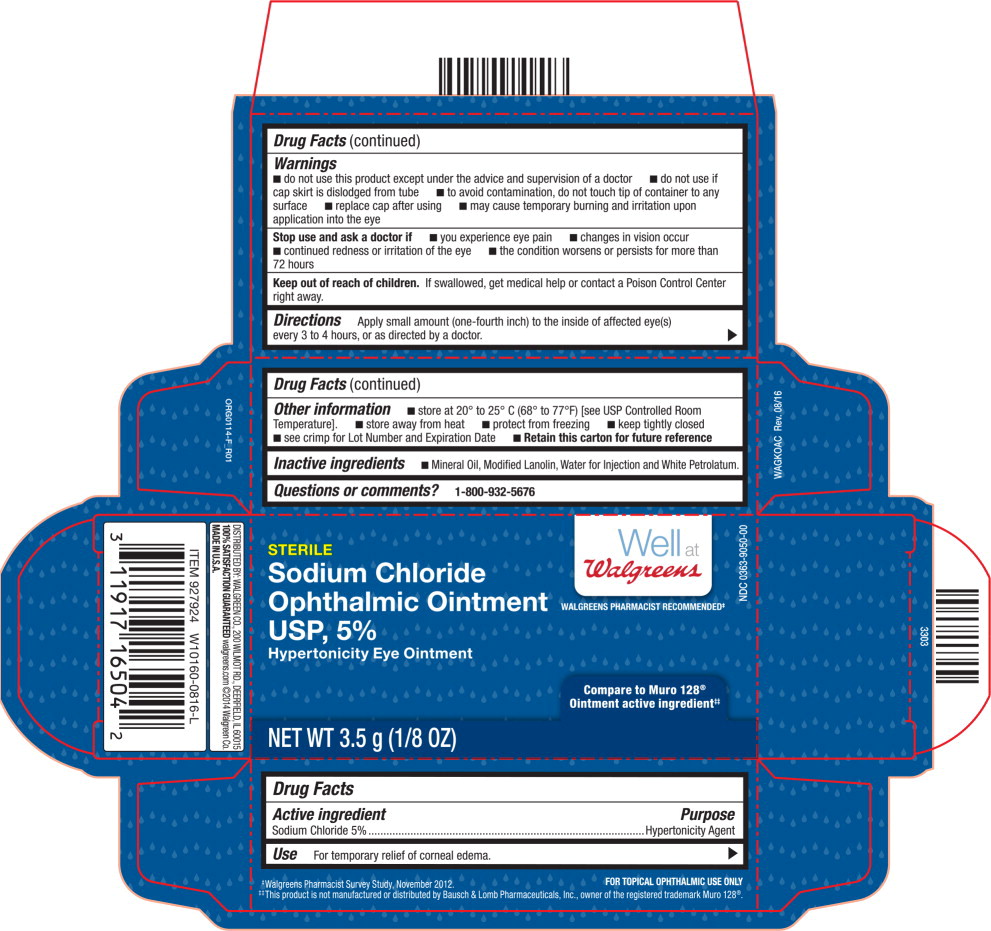 DRUG LABEL: Sodium Chloride
NDC: 0363-9050 | Form: OINTMENT
Manufacturer: Walgreens
Category: otc | Type: HUMAN OTC DRUG LABEL
Date: 20220127

ACTIVE INGREDIENTS: Sodium Chloride 50 mg/1 g
INACTIVE INGREDIENTS: Mineral Oil; Lanolin; Water; Petrolatum

Drug Facts

Active ingredient

Sodium Chloride 5%

Purpose

Hypertonicity Agent

Use

For temporary relief of corneal edema.

Warnings

- do not use this product except under the advice and supervision of a doctor
- do not use if cap skirt is dislodged from tube
- to avoid contamination, do not touch tip of container to any surface
- replace cap after using
- may cause temporary burning and irritation upon application into the eye

Stop use and ask a doctor if

- you experience eye pain
- changes in vision occur
- continued redness or irritation of the eye
- the condition worsens or persists for more than 72 hours

Keep out of reach of children. If swallowed, get medical help or contact a Poison Control Center right away.

Directions

Apply small amount (one-fourth inch) to the inside of affected eye(s) every 3 to 4 hours, or as directed by a doctor.

Other Information

- store at 20° to 25° C (68° to 77°F) [see USP Controlled Room Temperature].
- store away from heat
- protect from freezing
- keep tightly closed
- see crimp for Lot Number and Expiration Date
- Retain this carton for future reference

Inactive ingredients

- Mineral Oil, Modified Lanolin, Water for Injection and White Petrolatum.

Questions or comments?

1-800-932-5676

Principal Display Panel Text for Container Label:

STERILE Well at

Sodium Chloride Walgreens

Ophthalmic Ointment NDC 0363-9050-00

USP, 5% NET WT 3.5 g (1/8 oz.)

Hypertonicity Eye Ointment

FOR OPHTHALMIC USE ONLY

Principal Display Panel Text for Carton Label:

STERILE Well at

Walgreens NDC 0363-9050-00

WALGREENS PHARMACIST RECOMMENDED≠

Sodium Chloride

Ophthalmic Ointment

USP, 5%

Hypertonicity Eye Ointment

Compare to Muro 128®

Ointment active ingredient#

NET WT 3.5 g (1/8 OZ)